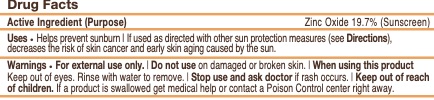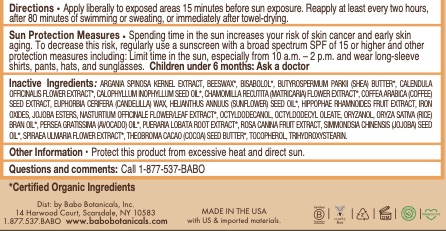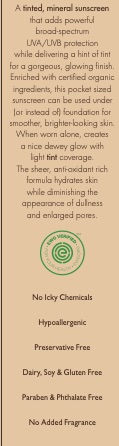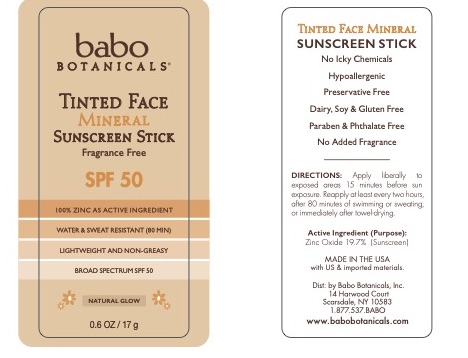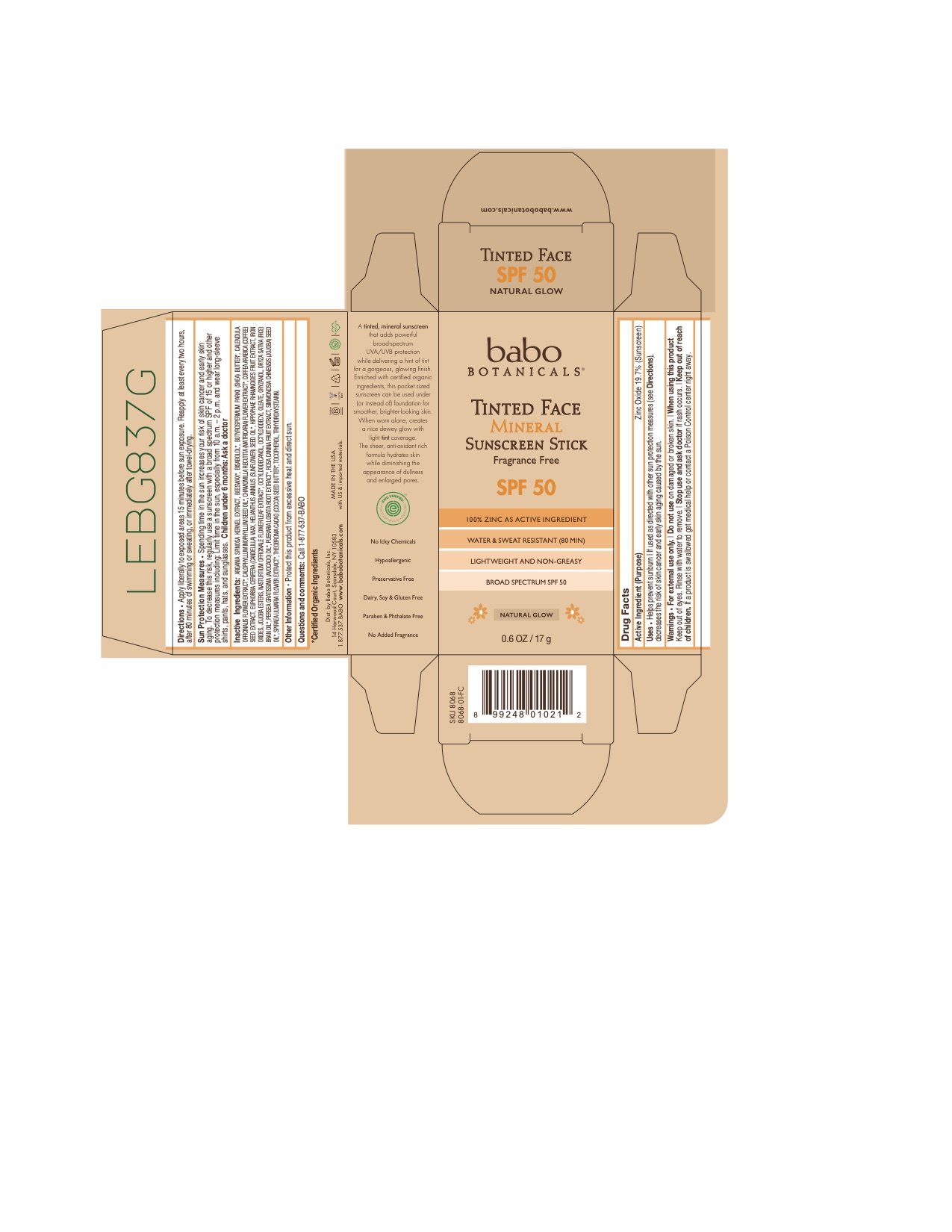 DRUG LABEL: SPF 50 Tinted Face Mineral Fragrance Free Sunscreen
NDC: 79265-8068 | Form: STICK
Manufacturer: Babo Botanicals, Inc.
Category: otc | Type: HUMAN OTC DRUG LABEL
Date: 20241212

ACTIVE INGREDIENTS: ZINC OXIDE 20.2115 g/100 g
INACTIVE INGREDIENTS: FERRIC OXIDE RED 0.5362 mL/100 g; PUERARIA MONTANA VAR. LOBATA ROOT 0.0015 mL/100 g; FILIPENDULA ULMARIA FLOWER 0.0015 mL/100 g; HIPPOPHAE RHAMNOIDES FRUIT 0.00125 mL/100 g; SUNFLOWER OIL 0.1875 mL/100 g; TRIHYDROXYSTEARIN 0.0092 mL/100 g; HYDROGENATED JOJOBA OIL, RANDOMIZED 0.9023 mL/100 g; NASTURTIUM OFFICINALE FLOWERING TOP 0.0015 mL/100 g; ROSA CANINA FRUIT 0.00125 mL/100 g; JOJOBA OIL 7.5 mL/100 g; COCOA BUTTER 3 mL/100 g; ARGANIA SPINOSA SEED 0.00125 mL/100 g; TOCOPHEROL 0.75 mL/100 g; AVOCADO OIL 15 mL/100 g; RICE BRAN OIL 23.07 mL/100 g; CANDELILLA WAX 9.5 mL/100 g; ARABICA COFFEE BEAN 0.00125 mL/100 g; OCTYLDODECYL OLEATE 8.75 mL/100 g; CALENDULA OFFICINALIS FLOWER 0.0015 mL/100 g; SHEA BUTTER 1 mL/100 g; CALOPHYLLUM TACAMAHACA SEED OIL 0.01 mL/100 g; CHAMOMILE 0.0015 mL/100 g; WHITE WAX 6 mL/100 g; LEVOMENOL 0.2 mL/100 g; OCTYLDODECANOL 0.3608 mL/100 g; ORYZANOL 3 mL/100 g

8068 Babo Botanicals SPF 50 Tinted Face Mineral Fragrance Free Sunscreen Stick

79265-8068-0 SPF 50 Tinted Face Mineral Fragrance Free Sunscreen Stick

This product is a mineral sunscreen semi solid stick manufactured pursuant to the sunscreen final monograph.

Primary Container Label

79265-8068-1

DRUG FACTS PANEL

79265-8068-0

ACTIVE INGREDIENTS

Zinc Oxide 20.2115%

USES

Uses • Helps prevent sunburn | If used as directed with other sun protection measures (see Directions), decreases the risk of skin cancer and early skin aging caused by the sun.

PURPOSE

SUNSCREEN

WARNINGS

Warnings • For external use only. | Do not use on damaged or broken skin. | When using this product Keep out of eyes. Rinse with water to remove. | Stop use and ask doctor if rash occurs. | Keep out of reach of children. If a product is swallowed get medical help or contact a Poison Control center right away

Do not use on damaged or broken skin

When using this product Keep out of eyes. Rinse with water to remove

STOP USE AND ASK A DOCTOR

Stop use and ask doctor if rash occurs

Keep out of reach of children. If a product is swallowed get medical help or contact a Poison Control center right away.

DIRECTIONS

DIRECTIONS Apply liberally to exposed areas 15 minutes before sun exposure. Reapply at least every two hours, after 80 minutes of swimming or sweating, or immediately after towel-drying

INACTIVE INGREDIENTS

ARGANIA SPINOSA KERNEL EXTRACT, BEESWAX*, BISABOLOL*, BUTYROSPERMUM PARKII (SHEA) BUTTER*, CALENDULA OFFICINALIS FLOWER EXTRACT*, CALOPHYLLUM INOPHYLLUM SEED OIL*, CHAMOMILLA RECUTITA (MATRICARIA) FLOWER EXTRACT*, COFFEA ARABICA (COFFEE) SEED EXTRACT, EUPHORBIA CERIFERA (CANDELILLA) WAX, HELIANTHUS ANNUUS (SUNFLOWER) SEED OIL*, HIPPOPHAE RHAMNOIDES FRUIT EXTRACT, IRON OXIDES, JOJOBA ESTERS, NASTURTIUM OFFICINALE FLOWER/LEAF EXTRACT*, OCTYLDODECANOL, OCTYLDODECYL OLEATE, ORYZANOL, ORYZA SATIVA (RICE) BRAN OIL*, PERSEA GRATISSIMA (AVOCADO) OIL*, PUERARIA LOBATA ROOT EXTRACT*, ROSA CANINA FRUIT EXTRACT, SIMMONDSIA CHINENSIS (JOJOBA) SEED OIL*, SPIRAEA ULMARIA FLOWER EXTRACT*, THEOBROMA CACAO (COCOA) SEED BUTTER*, TOCOPHEROL, TRIHYDROXYSTEARIN.

*CERTIFIED ORGANIC INGREDIENT

OTHER INFORMATION

Protect this product from excessive heat and direct sun.

QUESTIONS / COMMENTS?

Questions and comments: Call 1-877-537-BABO

INFORMATION PANEL

79265-8068-0 INFORMATION PANEL

Principal Display Panel

0.6 oz. 17 g 79265-8068-0